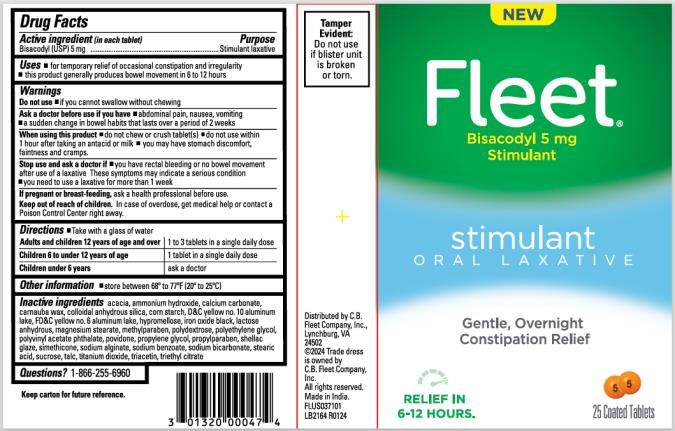 DRUG LABEL: Fleet
NDC: 0132-0401 | Form: TABLET, COATED
Manufacturer: C.B. Fleet Company, Inc.
Category: otc | Type: HUMAN OTC DRUG LABEL
Date: 20240621

ACTIVE INGREDIENTS: BISACODYL 5 mg/1 1
INACTIVE INGREDIENTS: ACACIA; AMMONIA; CALCIUM CARBONATE; CARNAUBA WAX; STARCH, CORN; D&C YELLOW NO. 10 ALUMINUM LAKE; FD&C YELLOW NO. 6; HYPROMELLOSES; FERROSOFERRIC OXIDE; ANHYDROUS LACTOSE; MAGNESIUM STEARATE; METHYLPARABEN; POLYDEXTROSE; POLYETHYLENE GLYCOL, UNSPECIFIED; Polyvinyl Acetate Phthalate; POVIDONE; PROPYLENE GLYCOL; PROPYLPARABEN; SHELLAC; SODIUM ALGINATE; SODIUM BENZOATE; SODIUM BICARBONATE; STEARIC ACID; SUCROSE; TALC; TITANIUM DIOXIDE; TRIACETIN; TRIETHYL CITRATE; DIMETHICONE

Fleet Oral Lax Bisacodyl 0132-0401

Active ingredient (in each tablet)

Bisacodyl USP 5 mg

Purpose

Stimulant laxative

Uses

- for temporary relief of occasional constipation and irregularity
- this product generally produces bowel movement in 6 to 12 hours

Warnings

Do not use

if you cannot swallow without chewing

Ask a doctor before use if you have

- abdominal pain, nausea or vomiting
- a sudden change in bowel habits that lasts more than 2 weeks

When using this product

- do not chew or crush tablet(s)
- do not use within 1 hour after taking an antacid or milk
- you may have stomach discomfort, faintness and cramps

Stop use and ask a doctor if

- you have rectal bleeding or no bowel movement after use of a laxative

These symptoms may indicate a serious condition.

- you need to use a laxative for more than 1 week

If pregnant or breast-feeding,

ask a health professional before use.

Keep out of reach of children.

In case of overdose, get medical help or contact a Poison Control Center right away.

Directions

- Take with a glass of water

Adults and children 12 years of age and over | 1 to 3 tablets in a single daily dose
Children 6 to under 12 years of age | 1 tablet in a single daily dose
Children under 6 years of age | ask a doctor

Other information

- store between 68º to 77ºF (20º to 25ºC)

Tamper Evident: Do not use if blister unit is broken or torn

Inactive ingredients

acacia, ammonium hydroxide, calcium carbonate, carnauba wax, colloidal anhydrous silica, corn starch, D&C yellow no. 10 aluminum lake, FD&C yellow no. 6 aluminum lake, hypromellose, iron oxide black, lactose anhydrous, magnesium stearate, methylparaben, polydextrose, polyethylene glycol, polyvinyl acetate phthalate, povidone, propylene glycol, propylparaben, shellac glaze, simethicone, sodium alginate, sodium benzoate, sodium bicarbonate, stearic acid, sucrose, talc, titanium dioxide, triacetin, triethyl citrate

Questions?

Call 1-866-255-6960

Principal Display Panel

Fleet

Bisacodyl 5 mg Stimulant

stimulant

oral laxative

25 coated tablets